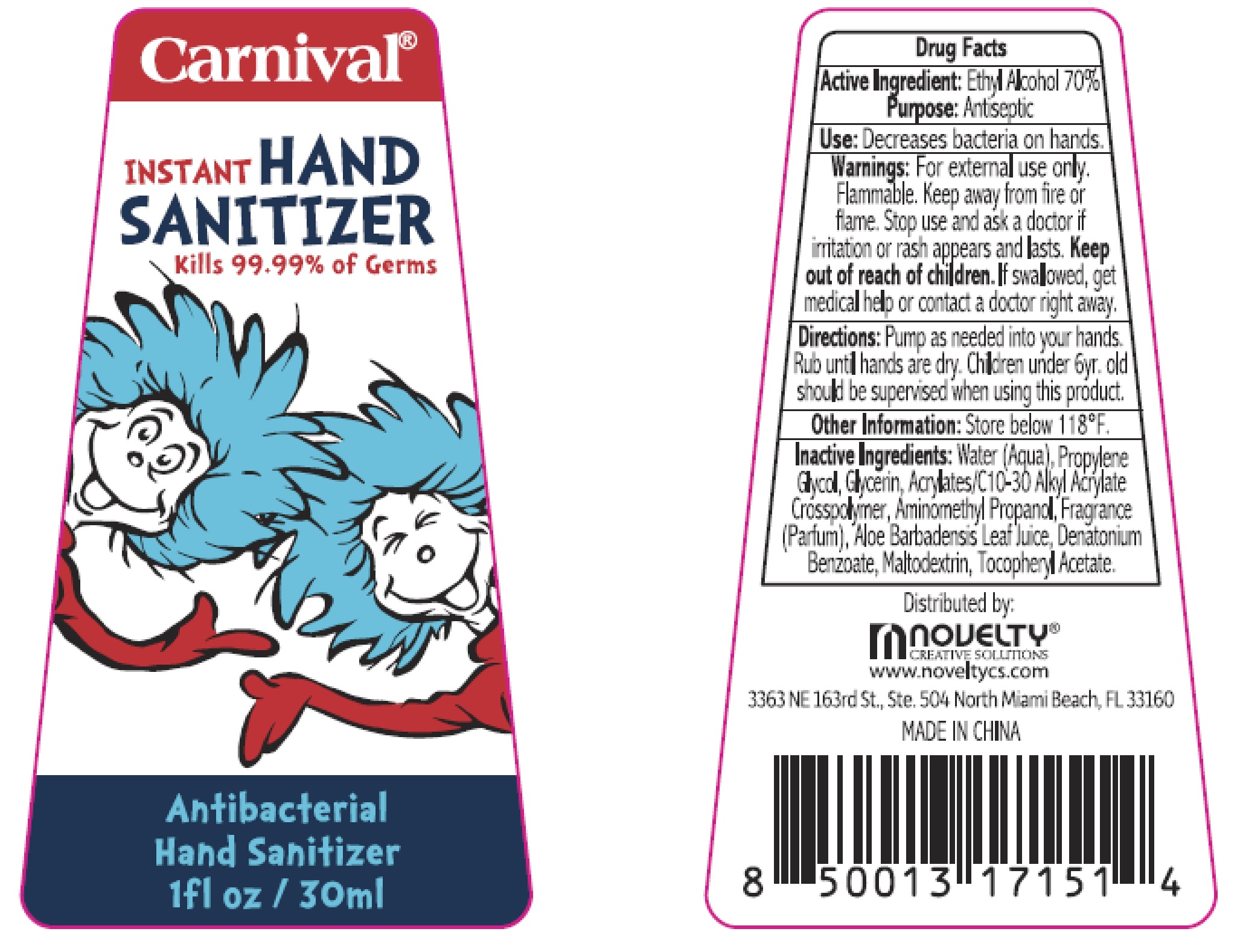 DRUG LABEL: INSTANT HAND SANITIZER
NDC: 72180-101 | Form: GEL
Manufacturer: Novelty Creative Solutions, Inc.
Category: otc | Type: HUMAN OTC DRUG LABEL
Date: 20210112

ACTIVE INGREDIENTS: ALCOHOL 70 mL/100 mL
INACTIVE INGREDIENTS: MALTODEXTRIN; .ALPHA.-TOCOPHEROL ACETATE; WATER; DENATONIUM BENZOATE; CARBOMER COPOLYMER TYPE A (ALLYL PENTAERYTHRITOL CROSSLINKED); ALOE VERA LEAF; AMINOMETHYLPROPANOL; GLYCERIN; PROPYLENE GLYCOL

Carnival
INSTANT HAND SANITIZER

Active Ingredient:

Ethyl Alcohol 70%

Purpose

Antiseptic

Use

Decrease bacteria on hands.

Warnings:

For external use only. Flammable. Keep away from fire or flame. Stop use and ask a doctor if irritation or rash appears or lasts.

Keep out of reach of children

If swallowed, get medical help or contact a doctor right away.

Directions

Pump as needed into your hands. Rub until hands are dry. Children under 6yr. old should be supervised when using this product.

Other Information:

Store below 118°F.

Inactive Ingredients:

Water(Aqua), Propylene Glycol, Glycerin, Acrylates/C10-30 Alkyl Acrylate Crosspolymer, Aminomethyl Propanol, Fragrance, Fragrance(Parfum), Aloe Barbadensis Leaf Juice, Denatonium Benzoate, Maltodextrin, Tocopheryl Acetate.